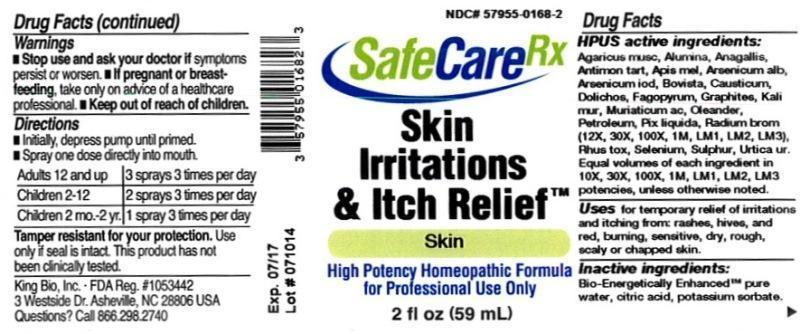 DRUG LABEL: Skin Irritations and Itch Relief
NDC: 57955-0168 | Form: LIQUID
Manufacturer: King Bio Inc.
Category: homeopathic | Type: HUMAN OTC DRUG LABEL
Date: 20150227

ACTIVE INGREDIENTS: ARSENIC TRIOXIDE 10 [hp_X]/59 mL; AMANITA MUSCARIA FRUITING BODY 10 [hp_X]/59 mL; ALUMINUM OXIDE 10 [hp_X]/59 mL; ANAGALLIS ARVENSIS 10 [hp_X]/59 mL; ANTIMONY POTASSIUM TARTRATE 10 [hp_X]/59 mL; APIS MELLIFERA 10 [hp_X]/59 mL; ARSENIC TRIIODIDE 10 [hp_X]/59 mL; LYCOPERDON UTRIFORME FRUITING BODY 10 [hp_X]/59 mL; CAUSTICUM 10 [hp_X]/59 mL; MUCUNA PRURIENS FRUIT TRICHOME 10 [hp_X]/59 mL; FAGOPYRUM ESCULENTUM 10 [hp_X]/59 mL; GRAPHITE 10 [hp_X]/59 mL; POTASSIUM CHLORIDE 10 [hp_X]/59 mL; HYDROCHLORIC ACID 10 [hp_X]/59 mL; NERIUM OLEANDER LEAF 10 [hp_X]/59 mL; KEROSENE 10 [hp_X]/59 mL; PINE TAR 10 [hp_X]/59 mL; RADIUM BROMIDE 12 [hp_X]/59 mL; TOXICODENDRON PUBESCENS LEAF 10 [hp_X]/59 mL; SELENIUM 10 [hp_X]/59 mL; SULFUR 10 [hp_X]/59 mL; URTICA URENS 10 [hp_X]/59 mL
INACTIVE INGREDIENTS: WATER; ANHYDROUS CITRIC ACID; POTASSIUM SORBATE

Skin Irritations and Itch Relief™

ACTIVE INGREDIENT

Drug Facts__________________________________________________________________________________________________________

HPUS active ingredients: Arsenicum album, Agaricus muscarius, Alumina, Anagallis arvensis, Antimonium tartaricum, Apis mellifica, Arsenicum lodatum, Bovista, Causticum, Dolichos pruriens, Fagopyrum esculentum, Graphites, Kali muriaticum, Muriaticum acidum, Oleander, Petroleum, Pix liquida, Radium bromatum (12X, 30X,100X,1M,LM1,LM2, LM3), Rhus toxicodendron, Selenium metallicum, Sulphur, Urtica urens. Equal volumes of each ingredient in 10X, 30X, 100X, 1M, LM1, LM2, LM3 potencies, unless otherwise noted.

INDICATIONS AND USAGE

Uses for temporary relief of irritations and itching from: rashes, hives, and red, burning, sensitive, dry, rough, scaly or chapped skin.

Inactive Ingredients:

Bio-Energetically Enhanced™ pure water, citric acid and potassium sorbate.

Warnings

- Stop use and ask your doctor if symptoms persist or worsen.
- If pregnant or breast-feeding, take only on advice of a healthcare professional.

- Keep out of reach of children.

Directions

- Initially, depress pump until primed.
- Spray one dose directly into mouth.
- Adults 12 and up: 3 sprays 3 times per day
- Children 2-12: 2 sprays 3 times per day
- Children 2mo-2yr: 1 spray 3 times per day

OTHER SAFETY INFORMATION

Tamper resistant for your protection. Use only if safety seal is intact. This product has not been clinically tested.

PURPOSE

Uses for temporary relief of irritations and itching from: rashes, hives, and red, burning, sensitive, dry, rough, scaly or chapped skin.